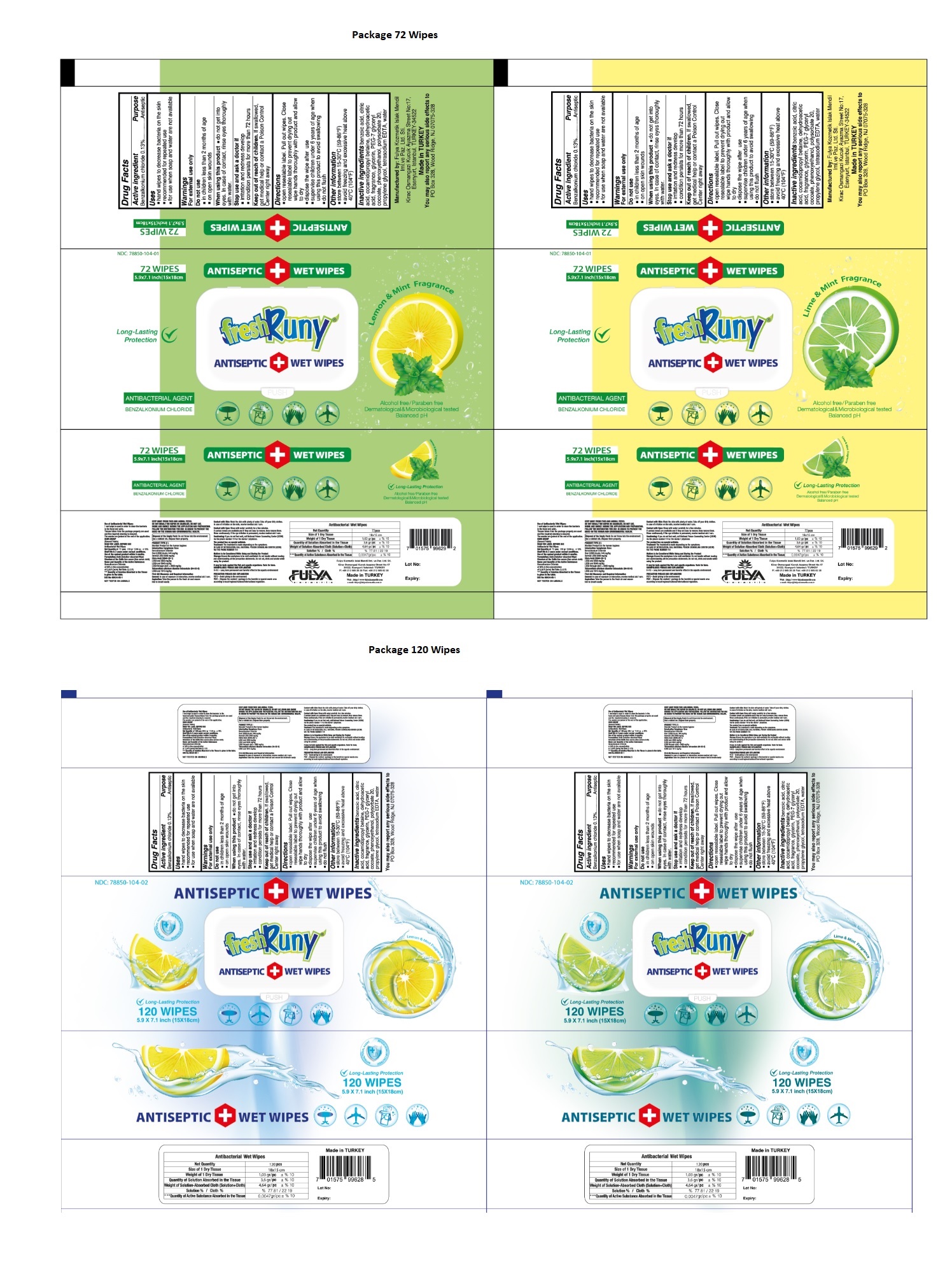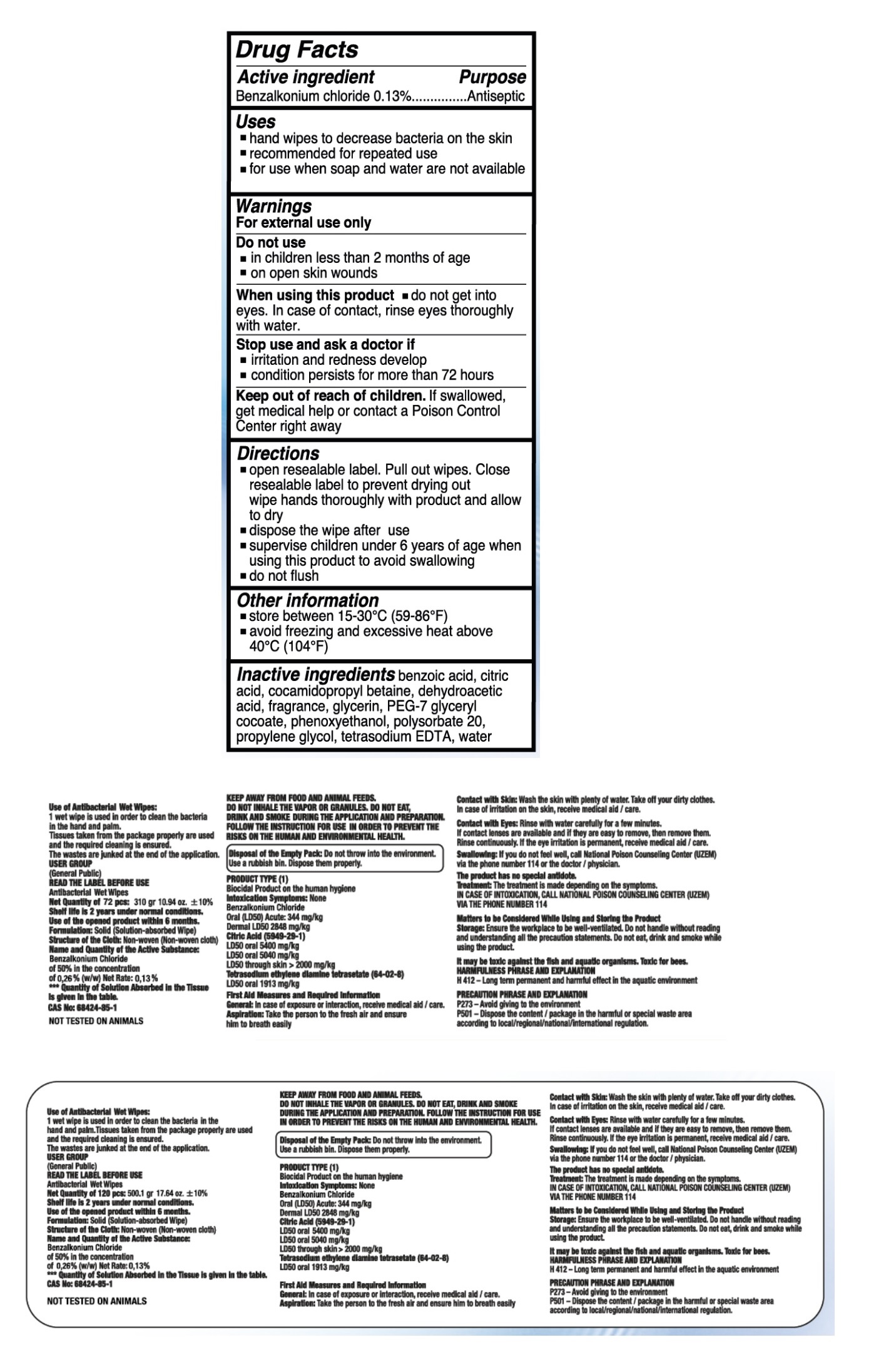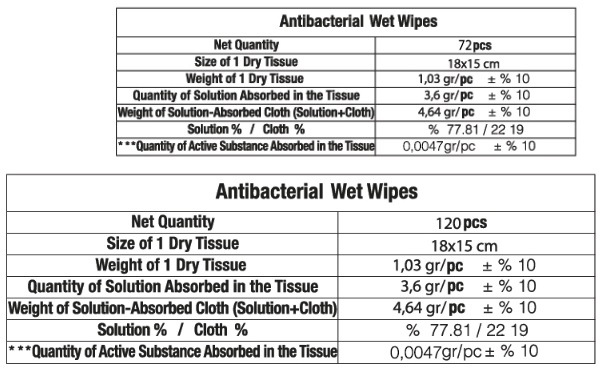 DRUG LABEL: Fresh Runy ANTISEPTIC WET WIPES
NDC: 78850-104 | Form: CLOTH
Manufacturer: FULYA KOZMETIK ISLAK MENDIL IMALAT VE PAZARLAMA LIMITED SIRKETI
Category: otc | Type: HUMAN OTC DRUG LABEL
Date: 20200903

ACTIVE INGREDIENTS: BENZALKONIUM CHLORIDE 0.13 g/100 g
INACTIVE INGREDIENTS: BENZOIC ACID; CITRIC ACID MONOHYDRATE; COCAMIDOPROPYL BETAINE; DEHYDROACETIC ACID; GLYCERIN; PEG-7 GLYCERYL COCOATE; PHENOXYETHANOL; POLYSORBATE 20; PROPYLENE GLYCOL; EDETATE SODIUM; WATER

Fresh Runy® ANTISEPTIC WET WIPES

Active ingredient

Benzalkonium chloride 0.13%

Purpose

Antiseptic

Uses

- hand wipes to decrease bacteria on the skin
- recommended for repeated use
- for use when soap and water are not available

Warnings

For external use only

Do not use

- in children less than 2 months of age
- on open skin wounds

When using this product • do not get into eyes. In case of contact, rinse eyes thoroughly with water

Stop use and ask a doctor if

- irritation and redness develop
- condition persists for more than 72 hours

Keep out of reach of children. If swallowed, get medical help or contact a Poison Control Center right away.

Directions

- open resealable label. Pull out wipes. Close resealable label to prevent drying out wipe hands thoroughly with product and allow to dry
- dispose the wipe after use
- supervise children under 6 years of age when using this product to avoid swallowing
- do not flush

Other information

- store between 15-30°C (59-86°F)
- avoid freezing and excessive heat above 40°C (104°F)

Inactive ingredients

benzoic acid, citric acid, cocamidopropyl betaine, dehydroacetic acid, fragrance, glycerin, PEG-7 glyceryl cocoate, phenoxyethanol, polysorbate 20, propylene glycol, tetrasodium EDTA, water,

ANTIBACTERIAL AGENT

Long-Lasting Protection

Alcohol free/ Paraben free

Dermatological & Microbiological tested

balanced pH

Manufactured by: Fulya Kozmetik Islak Mendil

Iml. ve Paz. Ltd. Sti.

Kirac Osmanagazi Kucuk Ayazma Street No: 17, Esenyurt, Istanbul, TURKEY - 34522

Made in TURKEY

You may also report any serious side effects to

PO Box 328, Wood Ridge, Nj 07075-328